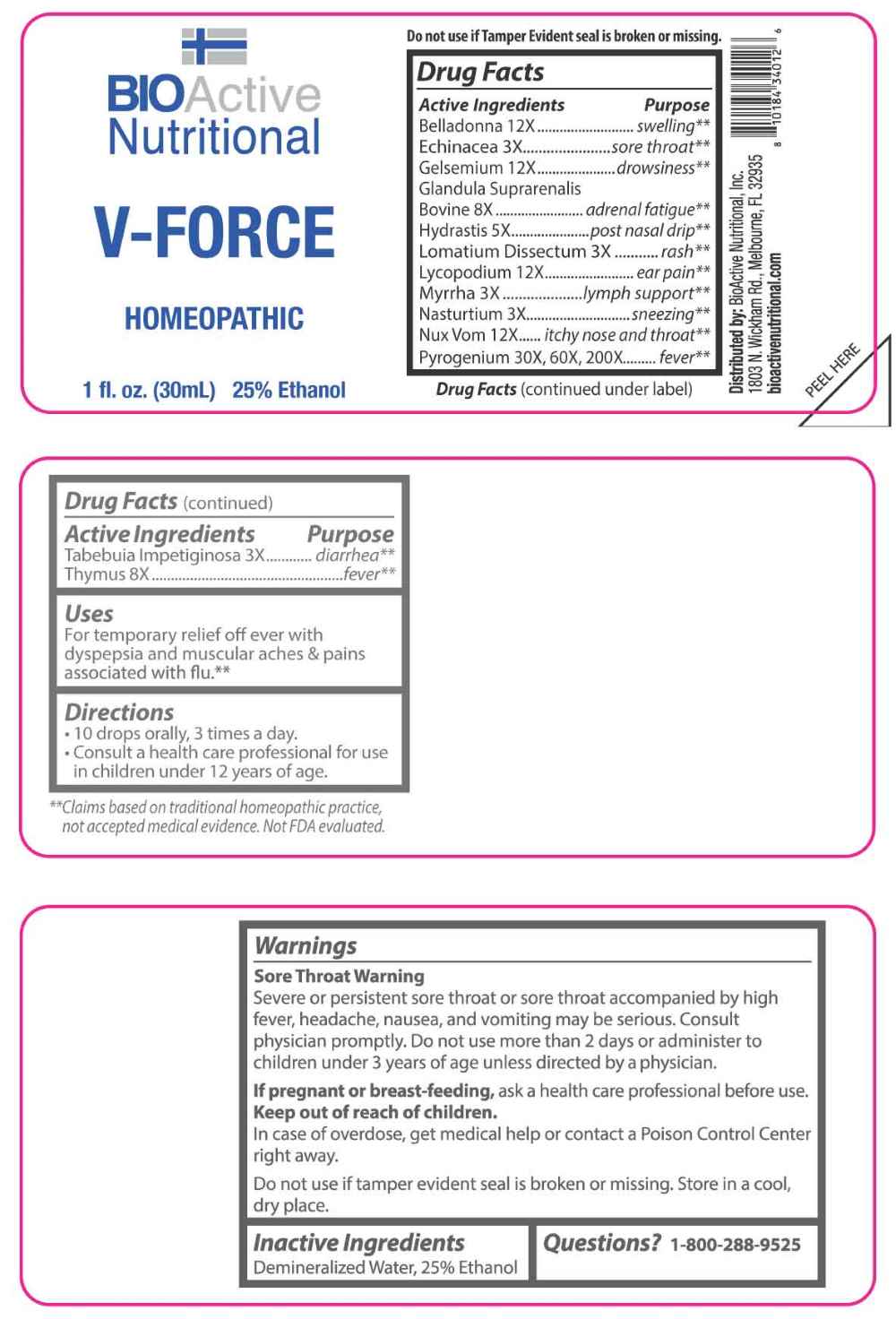 DRUG LABEL: V Force
NDC: 43857-0571 | Form: LIQUID
Manufacturer: BioActive Nutritional, Inc.
Category: homeopathic | Type: HUMAN OTC DRUG LABEL
Date: 20251121

ACTIVE INGREDIENTS: ECHINACEA ANGUSTIFOLIA WHOLE 3 [hp_X]/1 mL; LOMATIUM DISSECTUM ROOT 3 [hp_X]/1 mL; MYRRH 3 [hp_X]/1 mL; NASTURTIUM OFFICINALE 3 [hp_X]/1 mL; HANDROANTHUS IMPETIGINOSUS BARK 3 [hp_X]/1 mL; GOLDENSEAL 5 [hp_X]/1 mL; BOS TAURUS ADRENAL GLAND 8 [hp_X]/1 mL; BOS TAURUS THYMUS 8 [hp_X]/1 mL; ATROPA BELLADONNA 12 [hp_X]/1 mL; GELSEMIUM SEMPERVIRENS ROOT 12 [hp_X]/1 mL; LYCOPODIUM CLAVATUM SPORE 12 [hp_X]/1 mL; STRYCHNOS NUX-VOMICA SEED 12 [hp_X]/1 mL; RANCID BEEF 30 [hp_X]/1 mL
INACTIVE INGREDIENTS: WATER; ALCOHOL

DRUG FACTS:

ACTIVE INGREDIENTS:

Belladonna 12X, Echinacea Angustifolia 3X, Gelsemium Sempervirens 12X, Glandula Suprarenalis Bovine 8X, Hydrastis Canadensis 5X, Lomatium Dissectum 3X, Lycopodium Clavatum 12X, Myrrha 3X, Nasturtium Aquaticum 3X, Nux Vomica 12X, Pyrogenium 30X, 60X, 200X, Tabebuia Impetiginosa 3X, Thymus 8X.

PURPOSE:

Belladonna - swelling,** Echinacea Angustifolia – sore throat,** Gelsemium Sempervirens - drowsiness,** Glandula Suprarenalis Bovine – adrenal fatigue,** Hydrastis Canadensis – post nasal drip,** Lomatium Dissectum – rash,** Lycopodium Clavatum – ear pain,** Myrrha – lymph support,** Nasturtium Aquaticum - sneezing,** Nux Vomica – itchy nose and throat,** Pyrogenium - fever,** Tabebuia Impetiginosa - diarrhea,** Thymus – fever**

**Claims based on traditional homeopathic practice, not accepted medical evidence. Not FDA evaluated.

USES:

For temporary relief of fever with dyspepsia and muscular aches & pains associated with flu.**

**Claims based on traditional homeopathic practice, not accepted medical evidence. Not FDA evaluated.

WARNINGS:

Sore Throat Warning

Severe or persistent sore throat or sore throat accompanied by high fever, headache, nausea, and vomiting may be serious. Consult physician promptly. Do not use more than 2 days or administer to children under 3 years of age unless directed by a physician.

If pregnant or breast-feeding, ask a health care professional before use.

Keep out of reach of children. In case of overdose, get medical help or contact a Poison Control Center right away.

Do not use if tamper evident seal is broken or missing.

Store in a cool, dry place.

KEEP OUT OF REACH OF CHILDREN:

In case of overdose, get medical help or contact a Poison Control Center right away.

DIRECTIONS:

• 10 drops orally, 3 times a day.

• Consult a health care professional for use in children under 12 years of age.

INACTIVE INGREDIENTS:

Demineralized Water, 25% Ethanol

QUESTIONS:

Distributed by:

BioActive Nutritional, Inc.

1803 N. Wickham Rd.

Melbourne, FL 32935

bioactivenutritional.com

1-800-288-9525

PACKAGE LABEL DISPLAY:

BIOActive

Nutritional

V-FORCE

HOMEOPATHIC

1 fl. oz (30 mL)